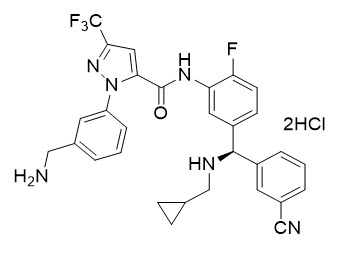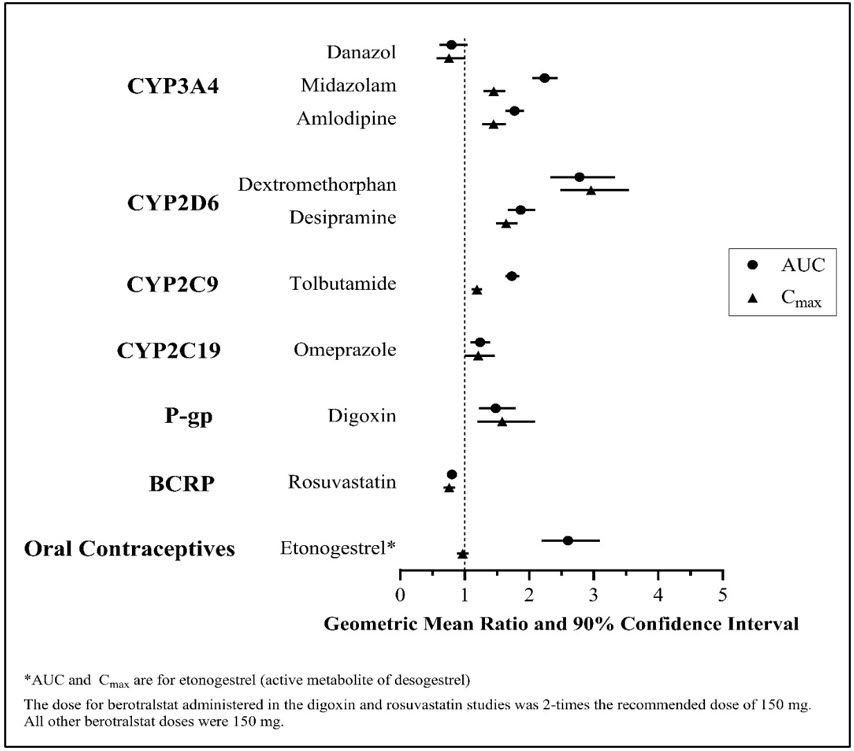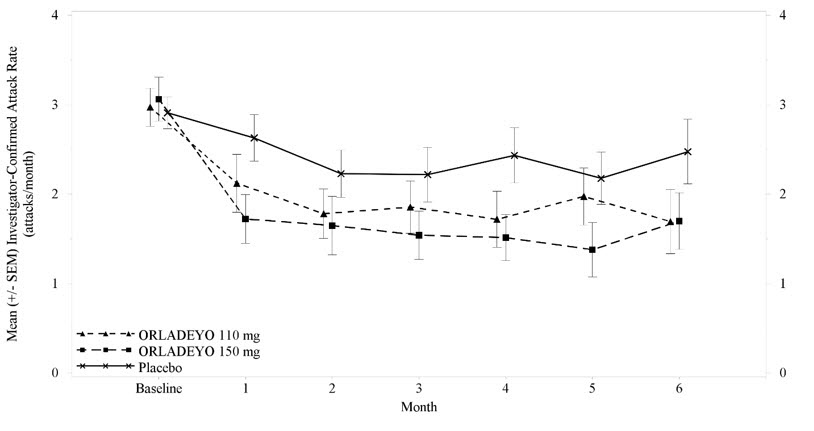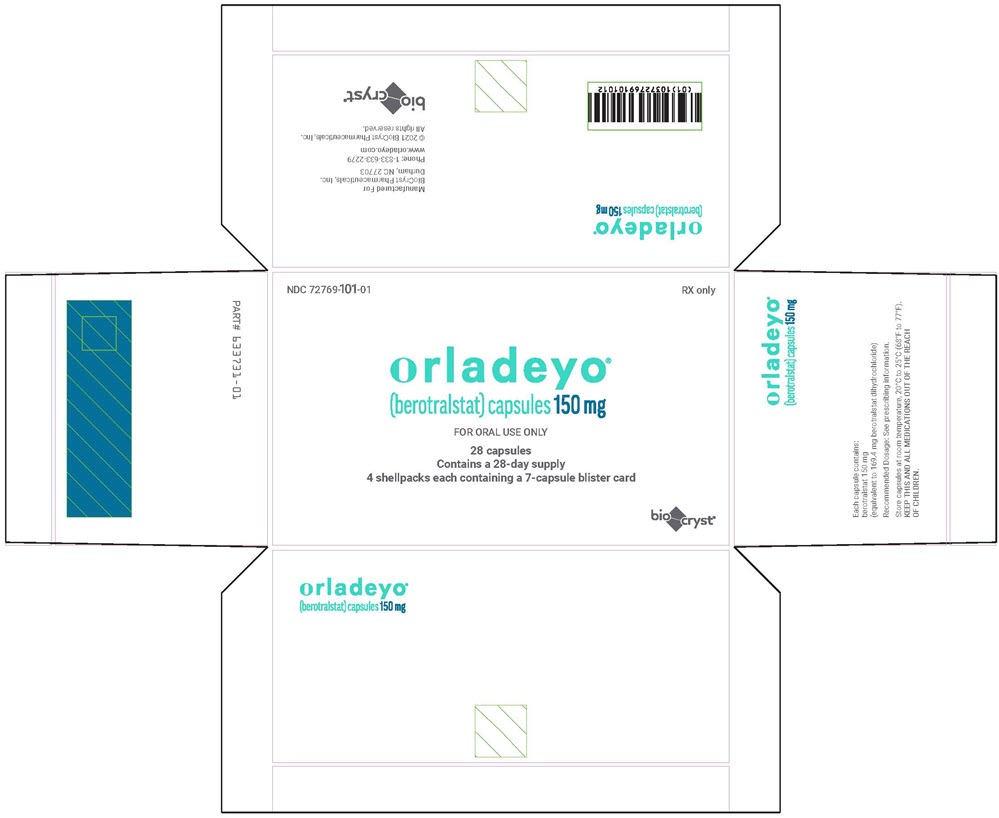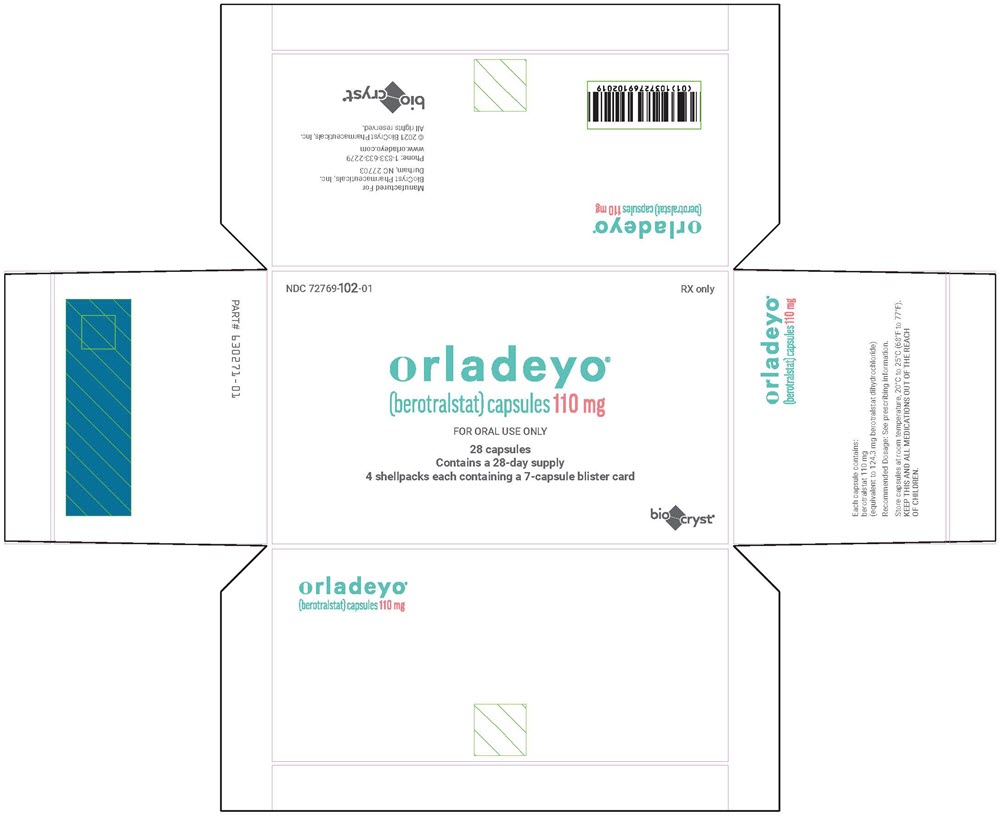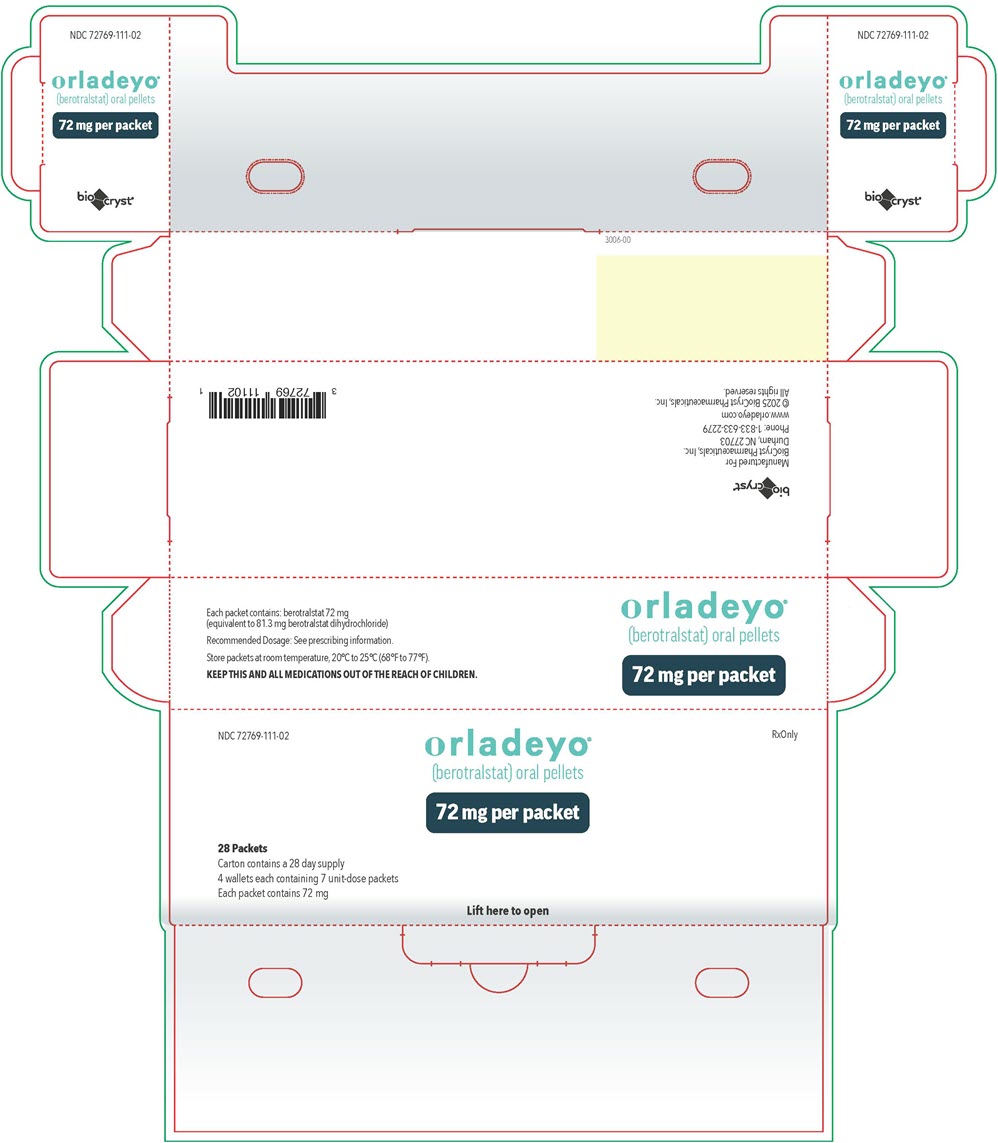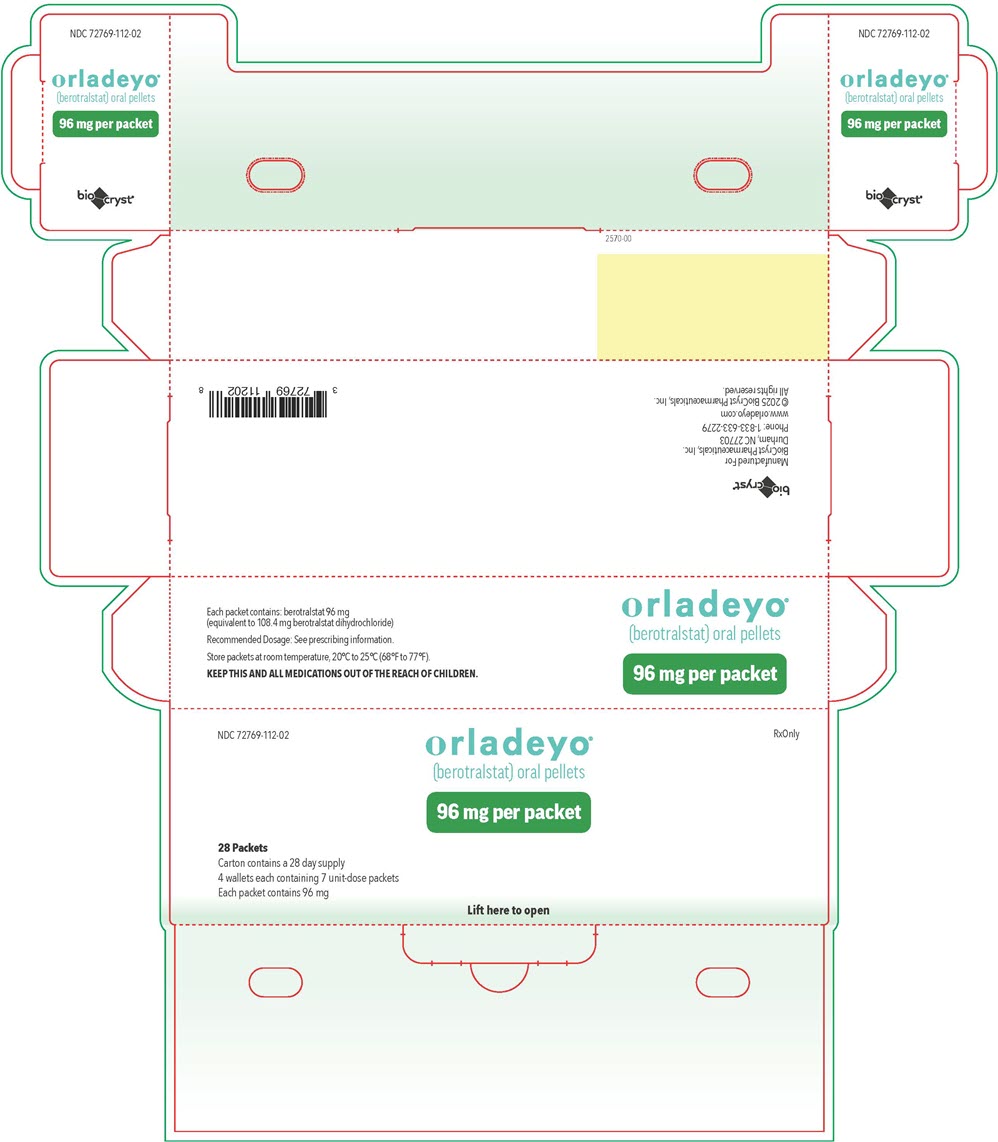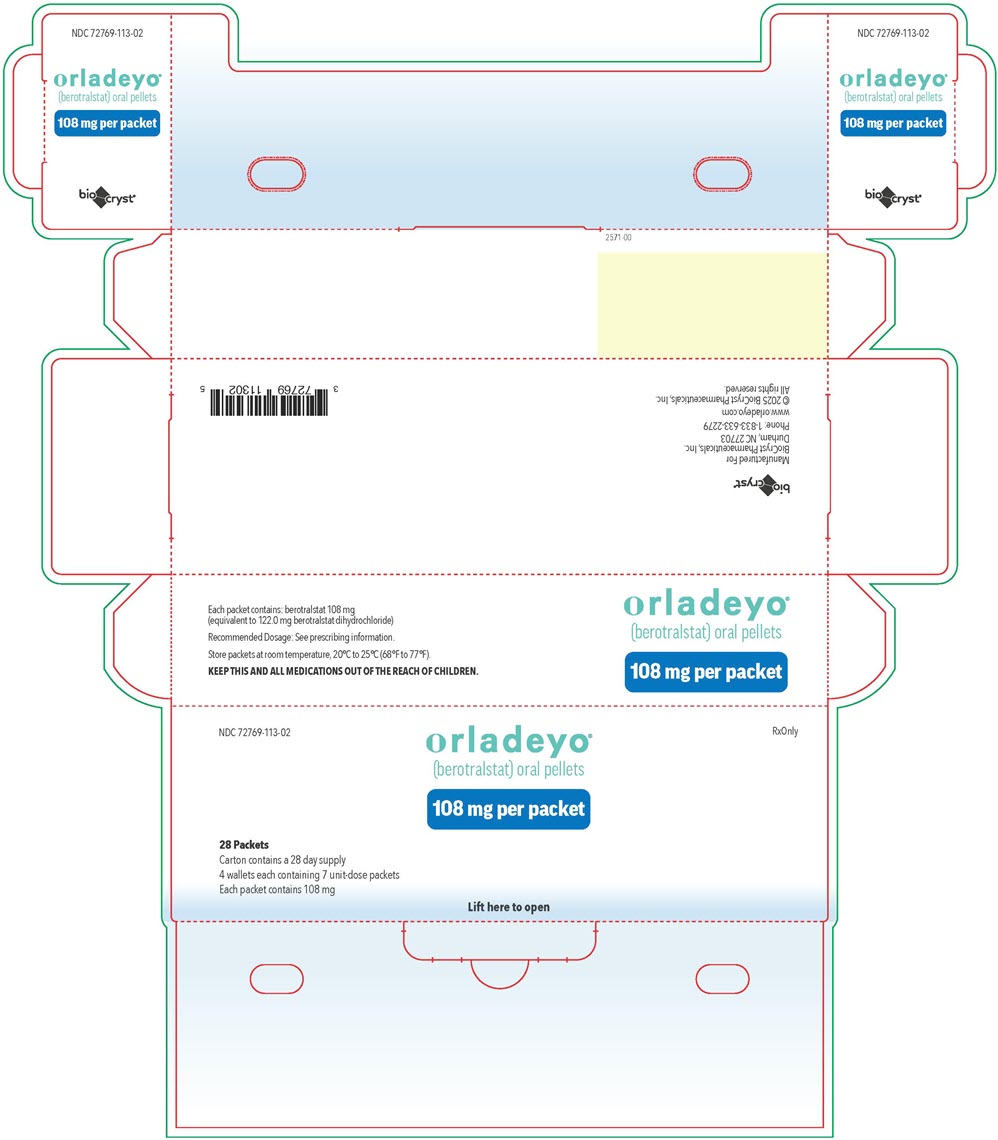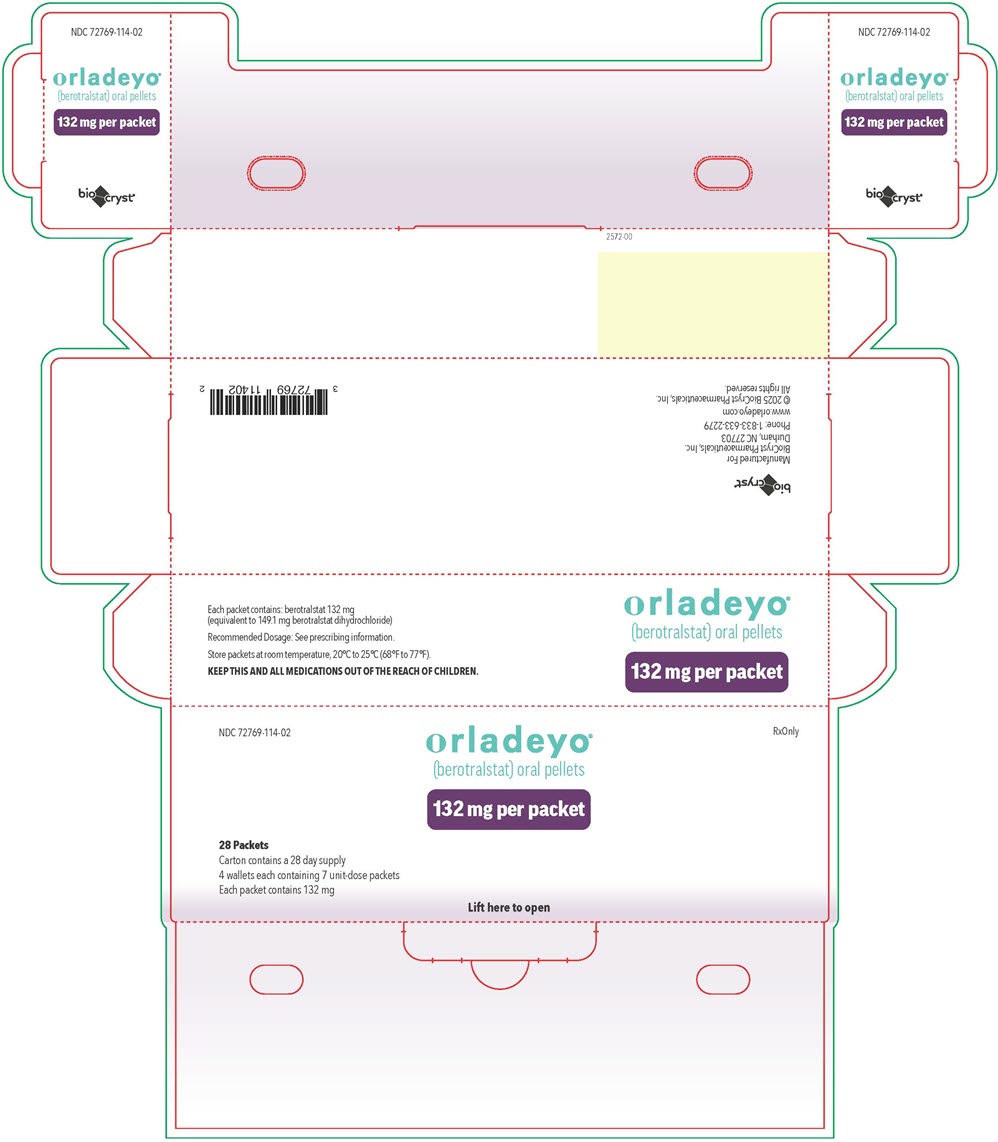 DRUG LABEL: Orladeyo
NDC: 72769-101 | Form: CAPSULE
Manufacturer: BioCryst Pharmaceuticals, Inc.
Category: prescription | Type: HUMAN PRESCRIPTION DRUG LABEL
Date: 20260213

ACTIVE INGREDIENTS: BEROTRALSTAT HYDROCHLORIDE 150 mg/1 1
INACTIVE INGREDIENTS: SILICON DIOXIDE; CROSPOVIDONE, UNSPECIFIED; MAGNESIUM STEARATE; STARCH, CORN

HIGHLIGHTS OF PRESCRIBING INFORMATION

These highlights do not include all the information needed to use ORLADEYO® safely and effectively. See full prescribing information for ORLADEYO.
ORLADEYO (berotralstat) capsules, for oral use
ORLADEYO (berotralstat) oral pellets
Initial U.S. Approval: 2020

RECENT MAJOR CHANGES

Indications and Usage (1) | 12/2025
Dosage and Administration (2.1, 2.2, 2.3, 2.4, 2.5) | 12/2025
Warnings and Precautions (5.1) | 12/2025

1 INDICATIONS AND USAGE

ORLADEYO is a plasma kallikrein inhibitor indicated for prophylaxis to prevent attacks of hereditary angioedema (HAE) in adults and pediatric patients 2 years and older. (1)

Limitations of Use:

ORLADEYO should not be used for treatment of acute HAE attacks. (1)

2 DOSAGE AND ADMINISTRATION

- Recommended dosage in adult and pediatric patients aged 12 years and older: 150 mg capsule orally once daily with food. (2.1)
- Recommended dosage in pediatric patients aged 2 to less than 12 years is based on body weight as follows (2.2, 2.5):

Weight | Recommended Dosage (oral pellets) | Administration Instructions
12 kg to less than 24 kg | 72 mg once daily | Pour directly in mouth and swallow immediately with non-acidic liquid, or, Sprinkle over 1 tablespoon (15 mL) of non-acidic soft food and consume immediately. A meal should be consumed just before or after administration.
24 kg to less than 32 kg | 96 mg once daily | Pour directly in mouth and swallow immediately with non-acidic liquid, or, Sprinkle over 1 tablespoon (15 mL) of non-acidic soft food and consume immediately. A meal should be consumed just before or after administration.
32 kg to less than 40 kg | 108 mg once daily | Pour directly in mouth and swallow immediately with non-acidic liquid, or, Sprinkle over 1 tablespoon (15 mL) of non-acidic soft food and consume immediately. A meal should be consumed just before or after administration.
40 kg or greater | 132 mg once daily | Pour directly in mouth and swallow immediately with non-acidic liquid, or, Sprinkle over 1 tablespoon (15 mL) of non-acidic soft food and consume immediately. A meal should be consumed just before or after administration.

- See full prescribing information for recommended dosage in patients with hepatic impairment and dosage modification in patients with persistent gastrointestinal adverse reactions. (2.3, 2.4)

3 DOSAGE FORMS AND STRENGTHS

- Capsules: 150 mg, 110 mg (3)
- Oral Pellets: 72 mg, 96 mg, 108 mg, or 132 mg in unit-dose packets (3)

4 CONTRAINDICATIONS

None. (4)

5 WARNINGS AND PRECAUTIONS

An increase in QTc interval prolongation can occur at dosages higher than the recommended dosage. Additional doses or doses of ORLADEYO higher than the recommended dosage are not recommended. (5.1)

6 ADVERSE REACTIONS

Most common adverse reactions (≥10%) are abdominal pain, vomiting, diarrhea, back pain, and gastroesophageal reflux disease. (6.1)

To report SUSPECTED ADVERSE REACTIONS, contact BioCryst Pharmaceuticals, Inc. at 1-833-633-2279 or FDA at 1-800-FDA-1088 or www.fda.gov/medwatch.

7 DRUG INTERACTIONS

- P-gp inducers: Avoid use with ORLADEYO. (7.1)
- CYP2D6, CYP3A4 or P-gp Substrates: When used concomitantly with ORLADEYO, closely monitor or modify the dosage of the substrates where minimal increases in concentration may lead to serious adverse reactions. (7.2, 12.3)

8 USE IN SPECIFIC POPULATIONS

- Avoid use of ORLADEYO in pediatric patients 2 years to less than 12 years of age with severe renal impairment. (8.6)
- ORLADEYO is not recommended in patients with end-stage renal disease. (8.6)

FULL PRESCRIBING INFORMATION

1 INDICATIONS AND USAGE

ORLADEYO® is indicated for prophylaxis to prevent attacks of hereditary angioedema (HAE) in adults and pediatric patients 2 years of age and older.

Limitations of Use:

The safety and effectiveness of ORLADEYO for the treatment of acute HAE attacks have not been established. ORLADEYO should not be used for treatment of acute HAE attacks. Additional doses or doses of ORLADEYO higher than the prescribed once-daily dose are not recommended due to the potential for QTc interval prolongation [see Warnings and Precautions (5.1)].

2 DOSAGE AND ADMINISTRATION

2.1 Recommended Dosage in Adults and Pediatric Patients 12 Years of Age and Older

The recommended dosage of ORLADEYO capsules for adults and pediatric patients 12 years of age and older is 150 mg taken orally once daily with food.

2.2 Recommended Dosage in Pediatric Patients 2 Years to Less than 12 Years of Age

The recommended dosage of ORLADEYO oral pellets for pediatric patients 2 years to less than 12 years of age is based on the patient's body weight as provided in Table 1. Take ORLADEYO orally with food (a meal should be consumed just before or after dosing) [see Dosage and Administration (2.5)].

Table 1: Recommended Dosage of ORLADEYO Oral Pellets by Body Weight in Pediatric Patients 2 Years to Less than 12 Years of Age
Body Weight (kg) | Recommended Dosage of ORLADEYO Oral Pellets
12 kg to less than 24 kg | 72 mg (one packet) once daily
24 kg to less than 32 kg | 96 mg (one packet) once daily
32 kg to less than 40 kg | 108 mg (one packet) once daily
40 kg or greater | 132 mg (one packet) once daily

2.3 Recommended Dosage in Patients with Hepatic Impairment

Mild Hepatic Impairment (Child-Pugh Class A)

Adult and Pediatric Patients 2 Years of Age and Older

- No dosage modification of ORLADEYO is recommended [see Use in Specific Populations (8.7) and Clinical Pharmacology (12.3)].

Moderate or Severe Hepatic Impairment (Child-Pugh Class B or C)

Adult and Pediatric Patients 12 Years of Age and Older

- Recommended dosage of ORLADEYO capsules is 110 mg taken orally once daily with food [see Use in Specific Populations (8.7) and Clinical Pharmacology (12.3)].

Pediatric Patients 2 Years to Less than 12 Years of Age

- Avoid use of ORLADEYO [see Use in Specific Populations (8.7)].

2.4 Dosage Modification in Patients with Persistent GI Adverse Reactions

Gastrointestinal (GI) reactions may occur in patients receiving ORLADEYO [see Adverse Reactions (6.1)].

- For adults and pediatric patients 12 years of age and older, if GI adverse reactions persist, consider a lower ORLADEYO capsules dosage of 110 mg once daily with food.
- For pediatric patients 2 to less than 12 years of age with persistent GI adverse reactions, consider the risks and benefits of continuing treatment with ORLADEYO.

2.5 Administration Instructions for Oral Pellets

Do not chew or crush ORLADEYO oral pellets because this will affect the film coating (taste masking) and result in bitter taste. Administer one packet of oral pellets as follows:

- Pour the entire contents of one packet directly into the mouth and swallow immediately with non-acidic liquid (e.g., water or milk).
  OR
- Sprinkle the entire contents of one packet over approximately one tablespoon (15 mL) of soft, non-acidic food and consume immediately. Food should be at or below room temperature. Examples of soft, non-acidic foods include pudding, mashed potatoes, creamed corn, pureed peas, pureed bananas, and pureed carrots. Acidic foods such as yogurt and applesauce should not be used because they can dissolve the film coating (taste masking) and result in a bitter taste. The film coating (taste masking) remains intact for 10 minutes. If the pellets are not consumed within 10 minutes of sprinkling over food, they should be discarded.

3 DOSAGE FORMS AND STRENGTHS

Capsules:

- 150 mg: a white opaque body with a black imprint "150" and a light blue opaque cap with a black imprint "BCX".
- 110 mg: light blue opaque body and cap with a white imprint "110" on body and a white imprint "BCX" on cap.

Oral Pellets:

- 72 mg, 96 mg, 108 mg, or 132 mg, white to off-white film-coated pellets in unit-dose packets.

4 CONTRAINDICATIONS

None.

5 WARNINGS AND PRECAUTIONS

5.1 Risk of QTc Interval Prolongation with Higher-Than-Recommended Dosages

ORLADEYO should not be used for treatment of acute attacks of HAE. Additional doses or doses of ORLADEYO higher than the recommended dosage are not recommended. An increase in QTc interval was observed in adults at dosages higher than 150 mg once daily and was concentration dependent [see Dosage and Administration (2) and Clinical Pharmacology (12.2)].

6 ADVERSE REACTIONS

The following clinically significant adverse reaction is described elsewhere in the labeling:

- QTc Interval Prolongation [see Warnings and Precautions (5.1)].

6.1 Clinical Trials Experience

Because clinical trials are conducted under widely varying conditions, adverse reaction rates observed in the clinical trials of a drug cannot be directly compared to rates in the clinical trials of another drug and may not reflect the rates observed in practice.

Adverse Reactions in Adult and Pediatric Patients 12 Years of Age and Older

The safety of ORLADEYO is primarily based on 24-week (Part 1) data from a 3-part, double-blind, parallel-group, placebo-controlled trial (Trial 1) in 120 patients with Type I or II HAE who were randomized and dosed with either ORLADEYO 110 mg, 150 mg, or placebo, once daily with food. After Week 24, patients who continued in the study received active treatment through 48 weeks.

In Trial 1, a total of 81 patients aged 12 years and older with HAE received at least one dose of ORLADEYO in Part 1. Overall, 66% of patients were female and 93% of patients were White with a mean age of 41.6 years. The proportion of patients who discontinued study drug prematurely due to adverse reactions was 7% and 3% for patients treated with ORLADEYO 110 mg and 150 mg, respectively, and 3% for placebo-treated patients. No deaths occurred in the trial.

The safety profile of ORLADEYO was generally similar across all subgroups of patients, including analysis by age, sex, and geographic region.

Table 2 shows adverse reactions occurring in ≥10% of adult and pediatric patients aged 12 years and older in any ORLADEYO treatment group that also occurred at a higher rate than in the placebo treatment group in Trial 1.

Table 2: Adverse Reactions Observed in ≥10% of Adult and Pediatric Patients Aged 12 Years and Older with HAE in Any ORLADEYO Treatment Group (Trial 1)
Adverse Reaction | Placebo (N=39) | ORLADEYO
Adverse Reaction | Placebo (N=39) | 110 mg (N=41) | 150 mg (N=40) | Total (N=81)
Adverse Reaction | n (%) | n (%) | n (%) | n (%)
Abdominal Pain [includes Abdominal pain, Abdominal discomfort, Abdominal pain upper, and Abdominal tenderness] | 4 (10) | 4 (10) | 9 (23) | 13 (16)
Vomiting | 1 (3) | 4 (10) | 6 (15) | 10 (12)
Diarrhea [includes Diarrhea and Frequent bowel movements] | 0 | 4 (10) | 6 (15) | 10 (12)
Back Pain | 1 (3) | 1 (2) | 4 (10) | 5 (6)
Gastroesophageal Reflux Disease | 0 | 4 (10) | 2 (5) | 6 (7)

Gastrointestinal adverse reactions, including abdominal pain, vomiting, and diarrhea occurred more frequently in patients receiving ORLADEYO 150 mg versus ORLADEYO 110 mg or placebo. These adverse reactions generally occurred early after initiation of treatment with ORLADEYO, became less frequent with time, and typically self-resolved. No patients in the ORLADEYO 150 mg dose group and 1 patient in the ORLADEYO 110 mg dose group discontinued treatment due to a gastrointestinal adverse reaction.

Less Common Adverse Reactions

Other adverse reactions that occurred in Part 1 of Trial 1 with an incidence between 5% to <10% and at a higher incidence in ORLADEYO-treated patients compared to placebo-treated patients included headache (9% versus 5%), fatigue (6% versus 3%), and flatulence (6% versus 3%).

A maculopapular drug rash was reported in less than 1% of patients treated with ORLADEYO. The rash resolved, including in patients who continued dosing.

Safety data are also available from 227 patients enrolled in an ongoing, open-label, long-term safety study (Trial 2) who received ORLADEYO 110 mg (N=100) or 150 mg (N=127) once daily with food and are consistent with the 24-week controlled safety data from Trial 1 (Part 1).

Laboratory Abnormalities

Transaminase Elevations

In Part 1 of Trial 1, one patient treated with ORLADEYO 150 mg discontinued treatment due to asymptomatic elevated transaminases (ALT >8x the upper limit of normal [ULN] and AST >3x ULN). Total bilirubin was normal. No patient receiving ORLADEYO 110 mg or placebo developed transaminase levels >3x ULN. In addition to this patient, 2 ORLADEYO-treated patients developed laboratory-related hepatic adverse reactions compared to 1 placebo-treated patient. No patient reported serious adverse reactions of elevated transaminases.

Adverse Reactions in Pediatric Patients 2 to Less than 12 Years of Age

The safety of ORLADEYO was evaluated in 29 pediatric patients aged 2 to <12 years with HAE in a multicenter, single-arm, open-label safety and pharmacokinetic study (Trial 3). Patients received ORLADEYO based on patient's body weight for at least 12 weeks, with 17 patients completing 48 weeks of treatment. No new safety signals were observed in these patients.

6.2 Postmarketing Experience

The following adverse reactions have been identified during postapproval use of ORLADEYO. Because these reactions are reported voluntarily from a population of uncertain size, it is not always possible to reliably estimate their frequency or establish a causal relationship to drug exposure.

Gastrointestinal Disorders: nausea

7 DRUG INTERACTIONS

7.1 Effect of Other Drugs on ORLADEYO

P-gp Inducers

Berotralstat is a substrate of P-gp and BCRP. P-gp inducers may decrease berotralstat plasma concentration, leading to reduced efficacy of ORLADEYO. Avoid concomitant use of P-gp inducers with ORLADEYO.

7.2 Effect of ORLADEYO on Other Drugs

CYP2D6 and CYP3A4 Substrates

ORLADEYO at a dose of 150 mg is a moderate inhibitor of CYP2D6 and CYP3A4. Concomitant use of ORLADEYO with CYP2D6 or CYP3A4 substrates can increase exposure of the CYP2D6 or CYP3A4 substrates and may increase the risk of adverse reactions associated with the substrates. If ORLADEYO is concomitantly used with CYP2D6 or CYP3A4 substrates where minimal increases in the concentration of the substrates may lead to serious adverse reactions, closely monitor or modify the dosage of the CYP2D6 or CYP3A4 substrate [see Clinical Pharmacology (12.3)]. Refer to the Prescribing Information of the CYP2D6 or CYP3A4 substrate.

Desogestrel

Concomitant use of ORLADEYO with desogestrel increases exposure to etonogestrel, the active metabolite of desogestrel, and may increase the risk of desogestrel-associated adverse reactions. Consider the benefits and risks when using ORLADEYO concomitantly with desogestrel [see Clinical Pharmacology (12.3)].

P-gp Substrates

ORLADEYO at 2-times the maximum recommended dose of 150 mg is a P-gp inhibitor and can increase exposure of P-gp substrates, leading to increased risk of adverse reactions associated with the substrates. Higher-than-recommended dosages of ORLADEYO are not recommended [see Warnings and Precautions (5.1)]. If ORLADEYO is concomitantly used with P-gp substrates where minimal increases in the concentration of the substrates may lead to serious adverse reactions, closely monitor or modify the dosage of the P-gp substrate [see Clinical Pharmacology (12.3)]. Refer to the Prescribing Information of the P-gp substrate.

8 USE IN SPECIFIC POPULATIONS

8.1 Pregnancy

Risk Summary

There are insufficient data in pregnant women available to inform drug-related risks with ORLADEYO use in pregnancy. Based on animal reproduction studies, no evidence of structural alterations was observed when berotralstat was administered orally to pregnant rats and rabbits during organogenesis at doses up to approximately 10- and 2-times, respectively, the maximum recommended human daily dose (MRHDD) in adults on an AUC basis (see Data).

The background risk of major birth defects and miscarriage for the indicated population is unknown. In the U.S. general population, the estimated background risk of major birth defects and miscarriage in clinically recognized pregnancies is 2% to 4% and 15% to 20%, respectively.

Data

Animal Data

In animal reproduction studies, oral administration of berotralstat to pregnant rats and rabbits during the period of organogenesis did not cause fetal structural alterations. The berotralstat dose in rats and rabbits was up to approximately 10- and 2-times, respectively, the MRHDD in adults (on an AUC basis at maternal doses of 75 and 100 mg/kg/day, respectively). In a pre- and postnatal development study in rats, oral administration of berotralstat to pregnant rats during the period of organogenesis and until delivery at doses up to 45 mg/kg/day (approximately 2-times of the MRHDD on a mg/m^2 basis) did not cause fetal structural alterations either. Berotralstat concentrations in the fetal blood were approximately 5% to 11% of the maternal blood.

8.2 Lactation

Risk Summary

There are no data on the presence of berotralstat in human milk, its effects on the breastfed infant, or its effects on milk production. However, when a drug is present in animal milk, it is likely that the drug will be present in human milk. Low levels of berotralstat were detected in the plasma of rat pups when dams were dosed with the drug orally during the lactation period. The berotralstat concentration in the pup plasma was approximately 2% of the maternal plasma (see Data).

The developmental and health benefits of breastfeeding should be considered along with the mother's clinical need for ORLADEYO and any potential adverse effects on the breastfed infant from ORLADEYO or from the underlying maternal condition.

Data

Animal Data

In the pre- and post-natal development study in rats, berotralstat was administered to dams during the pregnancy and lactation periods at doses up to 45 mg/kg/day (approximately 2-times of the MRHDD on a mg/m^2 basis). Berotralstat was detected in the plasma of pups during the lactation period. The berotralstat concentration in the pup plasma was approximately 2% of the maternal plasma. Both dams and pups at 45 mg/kg/day showed statistically significant decreases in body weight gain (p<0.05). No treatment-related effects were observed at 25 mg/kg/day (approximately equal to the MRHDD on a mg/m^2 basis).

8.4 Pediatric Use

The safety and effectiveness of ORLADEYO for prophylaxis to prevent attacks of hereditary angioedema have been established in pediatric patients aged 2 and older. The use of ORLADEYO in pediatric patients aged 12 to <18 years with HAE is supported by evidence from an adequate and well-controlled trial (Trial 1) that included adults and a total of 6 pediatric patients aged 12 to <18 years. The safety profile and attack rate in the study were similar to those observed in adults [see Adverse Reactions (6.1), Clinical Pharmacology (12.3), and Clinical Studies (14)]. An additional 10 pediatric patients aged 12 to <18 years were enrolled in the open-label study (Trial 2).

The use of ORLADEYO in pediatric patients aged 2 to <12 years with HAE is supported by efficacy data from an adequate and well-controlled study in adults and pediatric patients aged 12 years and older (Trial 1), and pharmacokinetic and safety data from 29 pediatric patients aged 2 to less than 12 years enrolled in a multicenter, single-arm, open-label study with additional support from population pharmacokinetic analyses. Pediatric patients aged 2 to less than 12 years received a dosage of ORLADEYO based on the patient's body weight, which showed no clinically significant difference in drug exposures from those observed in adults treated with ORLADEYO 150 mg [see Clinical Pharmacology (12.3)]. Pediatric patients aged 2 to less than 12 years were treated for at least 12 weeks, with 17 patients completing 48 weeks of treatment. No new safety signals were observed in pediatric patients aged 2 to less than 12 years [see Adverse Reactions (6.1)].

The safety and effectiveness of ORLADEYO have not been established in pediatric patients younger than 2 years of age.

8.5 Geriatric Use

Of the total number of patients in clinical studies of ORLADEYO, 9 patients were 65 years of age and over in Trial 1, and 5 patients were 65 years of age and over in Trial 2 (open-label safety study). No overall differences in safety or effectiveness of ORLADEYO have been observed between patients 65 years of age and older and younger adult patients [see Adverse Reactions (6.1), Clinical Pharmacology (12.3), and Clinical Studies (14)].

8.6 Renal Impairment

Mild to Moderate Renal Impairment

Adult and Pediatric Patients Aged 2 Years and Older

- No dosage modification of ORLADEYO is recommended [see Clinical Pharmacology (12.3)].

Severe Renal Impairment

Adult and Pediatric Patients Aged 12 Years and Older

- No dosage modification of ORLADEYO is recommended.

Pediatric Patients Aged 2 to Less than 12 Years

- Avoid use of ORLADEYO.

End-Stage Renal Disease

ORLADEYO has not been studied in patients with End-Stage Renal Disease (CLCR <15 mL/min or eGFR <15 mL/min/1.73 m^2 or patients requiring hemodialysis) and therefore is not recommended for use in these patient populations [see Clinical Pharmacology (12.3)].

8.7 Hepatic Impairment

Mild Hepatic Impairment (Child-Pugh Class A)

Adult and Pediatric Patients Aged 2 Years and Older

- No dosage modification of ORLADEYO is recommended [see Clinical Pharmacology (12.3)].

Moderate or Severe Hepatic Impairment (Child-Pugh B or C)

Adult and Pediatric Patients Aged 12 Years and Older

- The recommended dosage of ORLADEYO capsules is 110 mg once daily with food [see Dosage and Administration (2.3) and Clinical Pharmacology (12.3)].

Pediatric Patients Aged 2 Years and Older

- Avoid use of ORLADEYO.

11 DESCRIPTION

ORLADEYO (berotralstat) is a plasma kallikrein inhibitor. Berotralstat is presented as the dihydrochloride salt with the chemical name 1-[3-(aminomethyl)phenyl]-N-(5-{(R)-(3-cyanophenyl)[(cyclopropylmethyl)amino]methyl}-2-fluorophenyl)-3-(trifluoromethyl)-1H-pyrazole-5-carboxamide dihydrochloride. The chemical structure is:

Berotralstat dihydrochloride is a white to off-white powder that is soluble in water at pH ≤4. The molecular formula is C30H26F4N6O ∙ 2HCl and the molecular weight is 635.49 (dihydrochloride).

ORLADEYO (berotralstat) capsules contain 150 mg of berotralstat (equivalent to 169.4 mg berotralstat dihydrochloride) or 110 mg of berotralstat (equivalent to 124.3 mg berotralstat dihydrochloride) in hard gelatin capsules for oral administration. Each capsule contains the active ingredient berotralstat dihydrochloride and the inactive ingredients colloidal silicon dioxide, crospovidone, magnesium stearate, and pregelatinized starch.

ORLADEYO (berotralstat) oral pellets are white to off-white film-coated pellets for oral administration and enclosed in a unit-dose packet containing berotralstat 72 mg (equivalent to 81.3 mg berotralstat dihydrochloride), 96 mg (equivalent to 108.4 mg berotralstat dihydrochloride), 108 mg (equivalent to 122.0 mg berotralstat dihydrochloride), or 132 mg (equivalent to 149.1 mg of berotralstat dihydrochloride). Each unit-dose packet contains the active ingredient berotralstat dihydrochloride and the inactive ingredients colloidal silicon dioxide, crospovidone, magnesium stearate, and pregelatinized starch. The oral pellets film coating contains butylated methacrylate copolymer, silicon dioxide, sodium lauryl sulphate, stearic acid, talc, and titanium dioxide.

12 CLINICAL PHARMACOLOGY

12.1 Mechanism of Action

Berotralstat is a plasma kallikrein inhibitor that binds to plasma kallikrein and inhibits its proteolytic activity. Plasma kallikrein is a protease that cleaves high-molecular-weight kininogen (HMWK) to generate cleaved HMWK (cHMWK) and bradykinin, a potent vasodilator that increases vascular permeability resulting in swelling and pain associated with HAE. In patients with HAE due to C1-inhibitor (C1-INH) deficiency or dysfunction, normal regulation of plasma kallikrein activity is not present, which leads to uncontrolled increases in plasma kallikrein activity and results in angioedema attacks. Berotralstat decreases plasma kallikrein activity to control excess bradykinin generation in patients with HAE.

12.2 Pharmacodynamics

Concentration-dependent inhibition of plasma kallikrein, measured as a reduction from baseline of specific enzyme activity, was demonstrated after oral administration of ORLADEYO once daily in patients with HAE.

Cardiac Electrophysiology

At the maximum recommended dosage of 150 mg once daily in adults, clinically significant QTc interval prolongation was not observed. At 3-times the maximum recommended dosage, the mean (upper 90% confidence interval) increase in QTcF was 15.9 msec (23.5 msec). The observed increase in QTcF was concentration dependent.

12.3 Pharmacokinetics

Following oral administration of berotralstat 150 mg once daily in adults, the geometric mean steady-state Cmax is 158 ng/mL (range: 110 to 234 ng/mL) and steady-state area under the curve over the dosing interval (AUCtau) is 2770 ng*hr/mL (range: 1880 to 3790 ng*hr/mL). Following oral administration of berotralstat 110 mg once daily, the geometric mean steady-state Cmax is 97.8 ng/mL (range: 63 to 235 ng/mL) and steady-state AUCtau is 1600 ng*hr/mL (range: 950 to 4170 ng*hr/mL).

Berotralstat exposure (Cmax and AUC) increases in a greater than dose-proportional manner and steady state is reached in approximately 6 to 12 days. Berotralstat accumulation at steady state is approximately 5-fold at the recommended dosage.

No clinically significant difference in the pharmacokinetics of berotralstat was observed between healthy adult subjects and patients with HAE.

Absorption

The median time to maximum plasma concentration (Tmax) of berotralstat when administered with food is 5 hours (range: 1 to 8 hours).

No clinically significant difference in ORLADEYO exposure was observed following oral administration of either the pellets or capsules at the recommended adult dosage for 7 days.

Effect of Food

No clinically significant differences in the Cmax and AUC of berotralstat were observed following administration with a high-fat meal, however the median Tmax was delayed by 3 hours, from 2 hours (fasted) to 5 hours (fed).

Distribution

Plasma protein binding is approximately 99%. After a single dose of radiolabeled berotralstat at 2-times the maximum recommended dosage of 150 mg, the blood to plasma ratio was approximately 0.92.

Elimination

The median elimination half-life of berotralstat is approximately 93 hours (range: 39 to 152 hours).

Metabolism

Berotralstat is metabolized by CYP2D6 and by CYP3A4 with low turnover in vitro. After a single oral dose of radiolabeled berotralstat at 2-times the maximum recommended dosage of 150 mg, berotralstat represented 34% of the total plasma radioactivity, with 8 metabolites, each accounting for between 1.8 and 7.8% of the total radioactivity.

Excretion

After a single oral dose of radiolabeled berotralstat at 2-times the maximum recommended dosage of 150 mg, approximately 9% was excreted in urine (3.4% unchanged; range: 1.8 to 4.7%) and 79% was excreted in feces.

Specific Populations

In adults and pediatric patients 12 to <18 years of age, no clinically significant differences in the pharmacokinetics of ORLADEYO were observed based on age (12 to 74 years), sex, race, and body weight.

Pediatric Patients

Based on population pharmacokinetic analyses that included pediatric patients 12 to <18 years of age, exposure at steady state following oral administration of berotralstat 150 mg once daily was approximately 20% higher compared to adults. The higher exposure in pediatric patients 12 to <18 years of age is not considered to be clinically significant.

Based on population pharmacokinetics analyses that included pediatric patients 2 to <12 years of age, body weight was the only covariate with a clinically significant impact on the systemic exposure of berotralstat. In pediatric patients 2 to <12 years of age at the recommended dosage based on body weight, median Cmax at steady state is expected to be up to 24% higher compared to adults. However, this difference is not considered to be clinically significant [see Dosage and Administration (2.2) and Use in Special Populations (8.4)].

Patients with Renal Impairment

The pharmacokinetics of a single oral dose of berotralstat at 1.33-times the highest recommended dosage of 150 mg were studied in adult subjects with severe renal impairment (CLCR less than 30 mL/min, estimated by Cockcroft-Gault). When compared to a concurrent cohort with normal renal function (CLCR greater than 90 mL/min, estimated by Cockcroft-Gault), no clinically significant difference was observed; Cmax was increased by 47%, while AUC0-last was increased by 14% [see Use in Specific Populations (8.6)].

The pharmacokinetics of berotralstat has not been studied in patients with End-Stage Renal Disease (CLCR less than 15 mL/min or eGFR less than 15 mL/min/1.73 m^2 or patients requiring hemodialysis).

Patients with Hepatic Impairment

The pharmacokinetics of a single 150 mg oral dose of berotralstat were studied in adult subjects with mild, moderate, and severe hepatic function (Child-Pugh Class A, B, and C, respectively). The pharmacokinetics of berotralstat were unchanged in subjects with mild hepatic impairment compared to subjects with normal hepatic function. In subjects with moderate hepatic impairment, Cmax was increased by 77%, while AUC0-inf was increased by 78%. In subjects with severe hepatic impairment, Cmax was increased by 27%, while AUC0-last was decreased by 5%. The median half-life of berotralstat was increased by 37% and 22% in patients with moderate and severe hepatic impairment, respectively, in comparison to healthy subjects. The percent of unbound berotralstat increased 2-fold from a mean of 1.2% in healthy subjects to a mean of 2.4% in subjects with severe hepatic impairment [see Use in Specific Populations (8.7)].

Drug Interaction Studies

Effect of Other Drugs on the Pharmacokinetics of ORLADEYO

Berotralstat is a P-gp and BCRP substrate. Cyclosporine, a P-gp and BCRP inhibitor, decreased berotralstat 150 mg Cmax by 7%, while AUC0-last and AUC0-inf increased by 27% and 24%, respectively.

Effect of ORLADEYO on the Pharmacokinetics of Other Drugs

Berotralstat 150 mg once daily is a moderate inhibitor of CYP2D6 and CYP3A4, and a weak inhibitor of CYP2C9 and CYP2C19.

At 2-times the maximum recommended dosage of 150 mg, berotralstat is an inhibitor of P-gp and is not an inhibitor of BCRP (rosuvastatin exposure was decreased by approximately 20%).

In a drug interaction study conducted in healthy females of reproductive potential (N=22), concomitant administration of berotralstat 150 mg once daily with 0.15 mg/0.03 mg desogestrel/ethinyl estradiol led to a 2.6-fold increase in the AUC0-last of etonogestrel, the active metabolite of desogestrel.

The effect of berotralstat on the pharmacokinetics of other drugs are presented in Figure 1 [see Drug Interactions (7.2)].

Figure 1: Effect of ORLADEYO on Concomitant Medications

13 NONCLINICAL TOXICOLOGY

13.1 Carcinogenesis, Mutagenesis, Impairment of Fertility

Carcinogenesis

Carcinogenicity of berotralstat was evaluated in a 2-year study in Wistar rats and a 26-week study in Tg.rasH2 transgenic mice. The berotralstat doses (oral gavage) were up to 20 and 50 mg/kg/day in rats and mice (approximately 5- and 10-times the MRHDD on a plasma AUC basis, respectively). No evidence of tumorigenicity was observed in either species.

Mutagenesis

Berotralstat tested negative in the in vitro bacterial reverse mutation assay (Ames test), the in vitro chromosomal aberration assay in human peripheral blood lymphocytes, and the in vivo rat micronucleus assay.

Impairment of Fertility

In a fertility study in rats, berotralstat at oral doses up to 45 mg/kg/day (approximately 2-times the MRHDD on a mg/m^2 basis) showed no effect on fertility in males or females.

14 CLINICAL STUDIES

The efficacy of ORLADEYO for the prevention of angioedema attacks in adult and pediatric patients 12 years of age and older with Type I or II HAE was demonstrated in Part 1 of a multicenter, randomized, double-blind, placebo-controlled, parallel-group trial (Trial 1 [NCT3485911]).

The trial included 120 adults and pediatric patients 12 to <18 years of age who experienced at least two investigator-confirmed attacks within the first 8 weeks of the run-in period and took at least one dose of study treatment. Patients were randomized into 1 of 3 parallel treatment arms, stratified by baseline attack rate, in a 1:1:1 ratio (ORLADEYO 110 mg, ORLADEYO 150 mg, or placebo by oral administration once daily, with food) for the 24-week treatment period (Part 1).

Patients discontinued other prophylactic HAE medications prior to entering the trial; however, all patients were allowed to use rescue medications for treatment of breakthrough HAE attacks.

A history of laryngeal angioedema attacks was reported in 74% of patients and 75% reported prior use of long-term prophylaxis. The median attack rate during the prospective run-in period (baseline attack rate) was 2.9/month. Seventy percent of patients enrolled had a baseline attack rate of ≥2 attacks/month.

ORLADEYO 150 mg and 110 mg produced statistically significant reductions in the rate of HAE attacks compared to placebo for the primary endpoint in the Intent-to-Treat (ITT) population as shown in Table 3. The percent reductions in HAE attack rate were greater with ORLADEYO 150 mg and 110 mg relative to placebo, regardless of attack rate during the run-in period.

Table 3. Primary Efficacy Endpoint (Trial 1): Reduction in HAE Attack Rate - ITT Population (Adult and Pediatric Patients 12 Years of Age and Older)
Outcome | ORLADEYO |  | Placebo
Outcome | 110 mg QD | 150 mg QD | Placebo
Outcome | N = 41 | N = 40 | N = 40 [One patient in the ITT analysis was randomized to placebo but was not treated.]
HAE Attack Rate, rate per 28 days [Statistical analysis based on a negative binomial regression model; number of attacks included as dependent variable, treatment included as fixed effect, baseline attack rate included as covariate, and logarithm of duration on treatment included as offset variable.] | 1.65 | 1.31 | 2.35
% Rate Reduction [Percent reduction relative to placebo.] (95% CI) | 30.0% (4.6, 48.7) | 44.2% (23.0, 59.5) | -
p-value | 0.024 | <0.001 | -

Reductions in attack rates were observed in the first month of treatment with ORLADEYO 150 mg and 110 mg and were sustained through 24 weeks as shown in Figure 2.

Figure 2. Mean (+/- SEM) HAE Attack Rate/Month Through 24 Weeks (Trial 1) - ITT Population (Adult and Pediatric Patients 12 Years of Age and Older)

Pre-defined exploratory endpoints included the proportion of responders to ORLADEYO, defined as at least a 50% relative reduction in HAE attacks during treatment compared with the baseline attack rate; 58% of patients who received ORLADEYO 150 mg and 51% of patients who received ORLADEYO 110 mg had a ≥50% reduction in their HAE attack rates compared to baseline versus 25% of placebo patients. In post hoc analyses, 50% and 23% of patients who received ORLADEYO 150 mg, and 27% and 10% of patients who received ORLADEYO 110 mg, had a ≥70% or ≥90% reduction in their HAE attack rates compared to baseline versus 15% and 8% of placebo-treated patients, respectively. The rate of HAE attacks rated as moderate or severe was reduced by 40% and 10% in patients who received ORLADEYO 150 mg and 110 mg, respectively, versus placebo-treated patients.

16 HOW SUPPLIED/STORAGE AND HANDLING

ORLADEYO (berotralstat) capsules and oral pellets are supplied as follows in Table 4:

Table 4. Dosage Form, Strength, and Package Configuration for ORLADEYO
Dosage Form | Strength | Description | Package Configuration | NDC
Capsule | 110 mg | light blue opaque body and cap with a white imprint "110" on body and a white imprint "BCX" on cap | A 28-day supply of ORLADEYO is provided in a carton containing 4 child-resistant shellpacks, each containing a 7-capsule blister card. Each carton contains a tamper-evident seal. Do not use if tamper-evident seal is broken or missing. | 72769-102-01
Capsule | 150 mg | white opaque body with a black imprint "150" and a light blue opaque cap with a black imprint "BCX" | A 28-day supply of ORLADEYO is provided in a carton containing 4 child-resistant shellpacks, each containing a 7-capsule blister card. Each carton contains a tamper-evident seal. Do not use if tamper-evident seal is broken or missing. | 72769-101-01
Pellets | 72 mg | white to off-white, film-coated pellets | A 28-day supply of ORLADEYO oral pellets is provided in a carton containing 4 wallets, each containing 7 child-resistant unit-dose packets. Each carton contains a tamper-evident seal. Do not use if tamper-evident seal is broken or missing. | 72769-111-02
Pellets | 96 mg | white to off-white, film-coated pellets | A 28-day supply of ORLADEYO oral pellets is provided in a carton containing 4 wallets, each containing 7 child-resistant unit-dose packets. Each carton contains a tamper-evident seal. Do not use if tamper-evident seal is broken or missing. | 72769-112-02
Pellets | 108 mg | white to off-white, film-coated pellets | A 28-day supply of ORLADEYO oral pellets is provided in a carton containing 4 wallets, each containing 7 child-resistant unit-dose packets. Each carton contains a tamper-evident seal. Do not use if tamper-evident seal is broken or missing. | 72769-113-02
Pellets | 132 mg | white to off-white, film-coated pellets | A 28-day supply of ORLADEYO oral pellets is provided in a carton containing 4 wallets, each containing 7 child-resistant unit-dose packets. Each carton contains a tamper-evident seal. Do not use if tamper-evident seal is broken or missing. | 72769-114-02

STORAGE AND HANDLING

Store at 20°C to 25°C (68°F to 77°F). Excursions permitted between 15°C and 30°C (59°F to 86°F) [see USP Controlled Room Temperature].

17 PATIENT COUNSELING INFORMATION

Advise the patient to read the FDA-approved patient labeling (Patient Information).

Inform patients of the risks and benefits of ORLADEYO before prescribing or administering to the patient.

Not for Acute Treatment of HAE Attacks

Advise patients to take their usual rescue medication to treat an acute attack of HAE. Inform patients that the safety and effectiveness of ORLADEYO has not been established as a treatment for acute HAE attacks [see Indications and Usage (1)].

QTc Prolongation with Higher Than Recommended Dosages

Advise patients that they should not take daily doses higher than their prescribed once-daily dose or additional doses of ORLADEYO to treat an acute attack of HAE due to risk of QTc interval prolongation [see Indications and Usage (1) and Warnings and Precautions (5.1)].

Administration Instructions for Oral Pellets

Instruct patients that ORLADEYO oral pellets should not be chewed or crushed because this will affect the film coating, which masks the bitter taste. Advise patients to take ORLADEYO oral pellets by pouring one packet directly into the mouth and swallowing with a non-acidic liquid (e.g., water or milk), or to sprinkle one packet over one tablespoon of soft, non-acidic food and consume immediately [see Dosage and Administration (2.5)].

Drug Interactions

Advise patients that ORLADEYO may interact with other drugs [see Drug Interactions (7) and Clinical Pharmacology (12.3)]. Advise patients to report to their healthcare provider the use of any other prescription or nonprescription medication or herbal products.

For more information, visit www.ORLADEYO.com

ORLADEYO® is a registered trademark of BioCryst Pharmaceuticals, Inc.

Manufactured for:
BioCryst Pharmaceuticals, Inc.
Durham, NC 27703

ORL:4PI

PATIENT INFORMATION

ORLADEYO® (or-luh-DAY-oh)
(berotralstat)
capsules, for oral use

ORLADEYO® (or-luh-DAY-oh)
(berotralstat)
oral pellets

What is ORLADEYO?

- ORLADEYO is a prescription medicine used to prevent attacks of Hereditary Angioedema (HAE) in adults and children 2 years of age and older.
- ORLADEYO is not used to treat an acute HAE attack.
- Do not take more than 1 dose of ORLADEYO a day because extra doses can cause heart rhythm problems.
- It is not known if ORLADEYO is safe and effective to treat an acute HAE attack.
- It is not known if ORLADEYO is safe and effective in children under 2 years of age.

Before you take ORLADEYO, tell your healthcare provider about all of your medical conditions, including if you:

- have liver problems or kidney problems.
- are pregnant or planning to become pregnant. It is not known if ORLADEYO can harm your unborn baby.
- are breastfeeding or plan to breastfeed. It is not known if ORLADEYO passes into your breastmilk. Talk to your healthcare provider about the best way to feed your baby while taking ORLADEYO.

Tell your healthcare provider about all of the medicines you take, including other medicines for HAE, prescription and over-the-counter medicines, vitamins, and herbal supplements.
Taking ORLADEYO with certain other medicines may affect the way other medicines work and other medicines may affect how ORLADEYO works.
Know the medicines you take. Keep a list of them to show your healthcare provider and pharmacist when you get a new medicine.

How should I take ORLADEYO?

- Take ORLADEYO exactly as your healthcare provider tells you to take it.
- Take ORLADEYO with food.
- ORLADEYO capsules (for adults and children ages 12 years and older): Take 1 capsule, by mouth, 1 time every day.
- ORLADEYO oral pellets (ages 2 years to under 12 years): Take 1 packet, by mouth, 1 time every day.
  - Eat a meal either right before or right after you take your dose.
  - Do not chew or crush the oral pellets because this will affect the film coating and result in bitter taste.
  - Hold the packet with the cut line on top.
  - Gently tap the packet to settle the oral pellets.
  - Open the packet along the cut line.
  - Take ORLADEYO oral pellets in 1 of the following ways:
    - Pour all the oral pellets in the packet directly into the mouth and swallow right away with a non-acidic liquid such as water or milk.
      or
    - Carefully sprinkle all the oral pellets in the packet over 1 tablespoon (about 15mL) of soft, non-acidic food and take right away. Food should be at or below room temperature.
      Examples of soft, non-acidic foods include pudding, mashed potatoes, creamed corn, pureed peas, pureed bananas, and pureed carrots.
  - To prevent the taste-masking coating from dissolving and resulting in a bitter taste:
    - Take the oral pellets within 10 minutes of being sprinkled over food. Throw the oral pellets away if not taken within 10 minutes of sprinkling over food.
    - Do not sprinkle the oral pellets on acidic foods such as yogurt and applesauce.

What are the possible side effects of ORLADEYO?
Taking more than 1 dose of ORLADEYO a day may cause serious side effects, including:

- heart rhythm problems. A heart rhythm problem called QTc interval prolongation can happen in people who take more than 1 dose of ORLADEYO a day. This condition can cause an abnormal heart beat. Do not take more than 1 dose of ORLADEYO a day.

The most common side effects of ORLADEYO include:

- abdominal pain

- vomiting

- diarrhea

- back pain

- heartburn

Less common side effects include increases in liver function tests. Rarely, some people had a brief, itchy rash.
These are not all of the possible side effects of ORLADEYO. For more information, ask your healthcare provider or pharmacist.
Call your doctor for medical advice about side effects. You may report side effects to FDA at 1-800-FDA-1088.

How should I store ORLADEYO?

- Store ORLADEYO at room temperature between 68ºF to 77ºF (20ºC to 25ºC).
- Each carton contains a tamper evident seal. Do not use ORLADEYO if the tamper evident seal is broken or missing.

Keep ORLADEYO and all medicines out of the reach of children.

General information about the safe and effective use of ORLADEYO.
Medicines are sometimes prescribed for purposes other than those listed in a Patient Information leaflet. Do not use ORLADEYO for a condition for which it was not prescribed. Do not give ORLADEYO to other people, even if they have the same symptoms that you have. It may harm them. You can ask your pharmacist or healthcare provider for information about ORLADEYO that is written for health professionals.

What are the ingredients in ORLADEYO?
ORLADEYO capsules:
Active ingredient: berotralstat dihydrochloride
Inactive ingredients: colloidal silicon dioxide, crospovidone, magnesium stearate, and pregelatinized starch

ORLADEYO oral pellets:
Active ingredient: berotralstat dihydrochloride
Inactive ingredients: colloidal silicon dioxide, crospovidone, magnesium stearate, and pregelatinized starch.
The oral pellets film-coating contains: butylated methacrylate copolymer, silicon dioxide, sodium lauryl sulphate, stearic acid, talc, and titanium dioxide.

Manufactured for: BioCryst Pharmaceuticals, Inc., Durham, NC 27703
ORLADEYO® is a registered trademark of BioCryst Pharmaceuticals, Inc.
© 2025 BioCryst. All rights reserved.
ORL:2PPI
For more information, visit www.ORLADEYO.com or call 1-833-633-2279.

This Patient Information has been approved by the U.S. Food and Drug Administration.

Issued: 12/2025

PRINCIPAL DISPLAY PANEL - 150 mg Capsule Blister Card Shellpack Carton

NDC 72769-101-01
RX only

orladeyo®
(berotralstat) capsules 150 mg

FOR ORAL USE ONLY

28 capsules
Contains a 28-day supply
4 shellpacks each containing a 7-capsule blister card

bio cryst®

PRINCIPAL DISPLAY PANEL - 110 mg Capsule Blister Card Shellpack Carton

NDC 72769-102-01
RX only

orladeyo®
(berotralstat) capsules 110 mg

FOR ORAL USE ONLY

28 capsules
Contains a 28-day supply
4 shellpacks each containing a 7-capsule blister card

bio cryst®

PRINCIPAL DISPLAY PANEL - 72 mg Pellet Packet Wallet Carton

NDC 72769-111-02

RxOnly

orladeyo®
(berotralstat) oral pellets

72 mg per packet

28 Packets
Carton contains a 28 day supply
4 wallets each containing 7 unit-dose packets
Each packet contains 72 mg

Lift here to open

PRINCIPAL DISPLAY PANEL - 96 mg Pellet Packet Wallet Carton

NDC 72769-112-02

RxOnly

orladeyo®
(berotralstat) oral pellets

96 mg per packet

28 Packets
Carton contains a 28 day supply
4 wallets each containing 7 unit-dose packets
Each packet contains 96 mg

Lift here to open

PRINCIPAL DISPLAY PANEL - 108 mg Pellet Packet Wallet Carton

NDC 72769-113-02

RxOnly

orladeyo®
(berotralstat) oral pellets

108 mg per packet

28 Packets
Carton contains a 28 day supply
4 wallets each containing 7 unit-dose packets
Each packet contains 108 mg

Lift here to open

PRINCIPAL DISPLAY PANEL - 132 mg Pellet Packet Wallet Carton

NDC 72769-114-02

RxOnly

orladeyo®
(berotralstat) oral pellets

132 mg per packet

28 Packets
Carton contains a 28 day supply
4 wallets each containing 7 unit-dose packets
Each packet contains 132 mg

Lift here to open